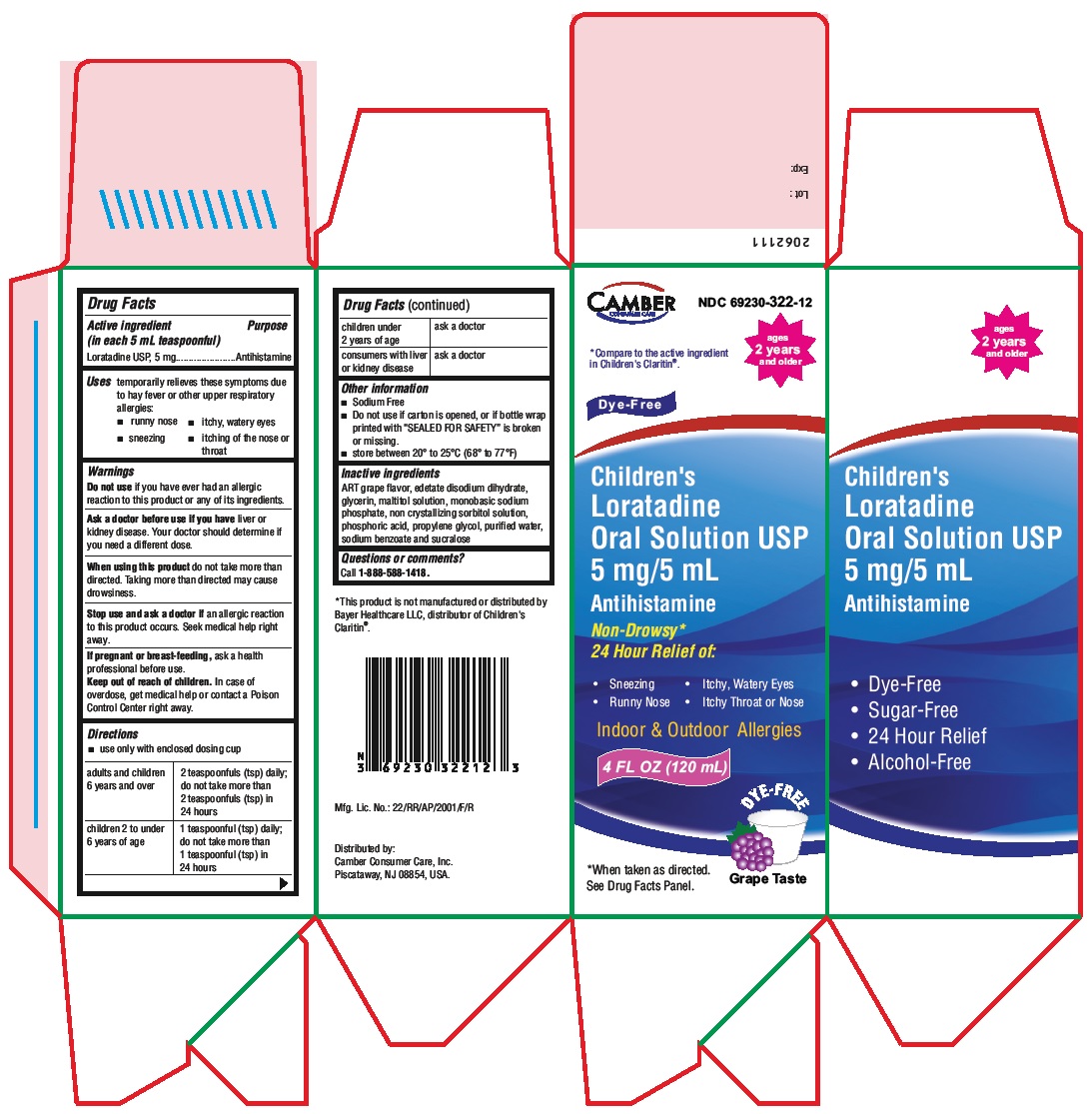 DRUG LABEL: Loratadine

NDC: 69230-322 | Form: SOLUTION
Manufacturer: Camber Consumer Care Inc
Category: otc | Type: HUMAN OTC DRUG LABEL
Date: 20210528

ACTIVE INGREDIENTS: LORATADINE 5 mg/5 mL
INACTIVE INGREDIENTS: EDETATE DISODIUM; GLYCERIN; MALTITOL; SODIUM PHOSPHATE, MONOBASIC; SORBITOL; PHOSPHORIC ACID; PROPYLENE GLYCOL; WATER; SODIUM BENZOATE; SUCRALOSE

Loratadine Oral Solution USP, 5mg/5 mL (OTC)

ACTIVE INGREDIENT(S)

(in each 5 mL teaspoonful)
Loratadine USP, 5mg

PURPOSE

Antihistamine

USE(S)

Temporarily relieves these symptoms due to hay fever or other upper respiratory allergies:

• runny nose
• itchy, watery eyes
• sneezing
• itching of the nose or throat

DO NOT USE

if you have ever had an allergic reaction to this product or any of its ingredients.

ASK A DOCTOR BEFORE USE IF YOU HAVE

liver or kidney disease. Your doctor should determine if you need a different dose.

WHEN USING THIS PRODUCT

do not take more than directed. Taking more than directed may cause drowsiness.

STOP USE AND ASK A DOCTOR IF

an allergic reaction to this product occurs. Seek medical help right away.

If pregnant or breast-feeding,

ask a health professional before use.

KEEP OUT OF REACH OF CHILDREN

In case of overdose, get medical help or contact a Poison Control Center right away.

DIRECTIONS

•use only with enclosed dosing cup

adults and children 6 years and over | 2 teaspoonfuls (tsp) daily; do not take more than 2 teaspoonfuls (tsp) in 24 hours
children 2 to under 6 years of age | 1 teaspoonful (tsp) daily; do not take more than 1 teaspoonful (tsp) in 24 hours
children under 2 years of age | ask a doctor
consumers with liver or kidney disease | ask a doctor

OTHER INFORMATION

• Sodium Free
• do not use if tape imprinted with 'SEALED FORYOUR PROTECTION' on top and bottom flaps of carton is not intact
• store between 20° to 25°C (68° to 77°F)

INACTIVE INGREDIENTS

ART grape flavor, edetate disodium dihydrate, glycerin, maltitol solution, monobasic sodium phosphate, non crystallizing sorbitol solution, phosphoric acid, propylene glycol, purified water, sodium benzoate and sucralose

QUESTIONS OR COMMENTS?

Call 1-888-588-1418
Distributed by:
Camber Consumer Care, Inc.
Piscataway, NJ 08854, USA.

PRINCIPAL DISPLAY PANEL

Loratadine Oral Solution USP, 5 mg/5mL 120 mL Carton Label